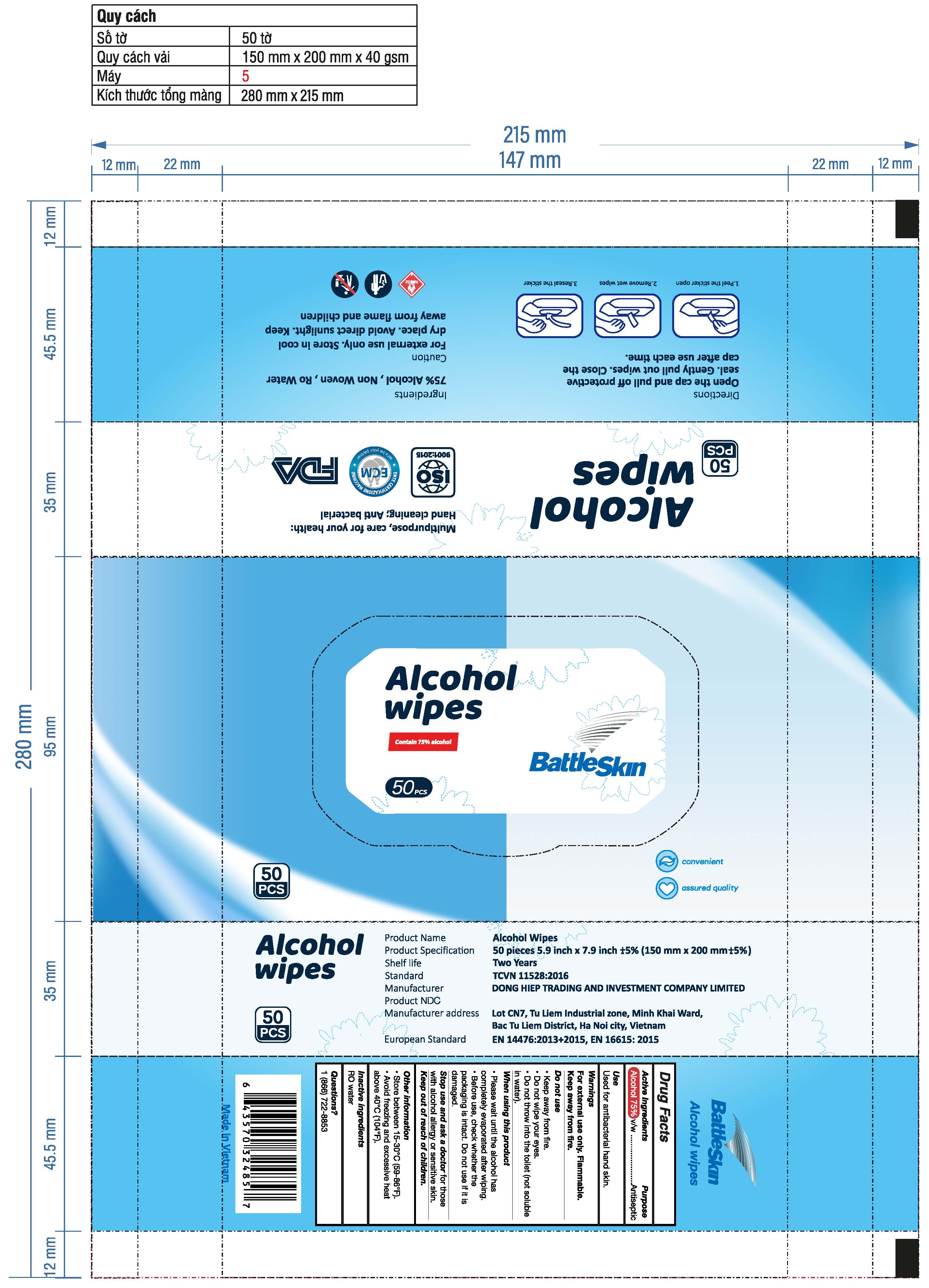 DRUG LABEL: Battle Skin Alcohol Wipes
NDC: 79366-103 | Form: CLOTH
Manufacturer: Dong Hiep Trading and Investment Co., Ltd
Category: otc | Type: HUMAN OTC DRUG LABEL
Date: 20201101

ACTIVE INGREDIENTS: ALCOHOL 75 mL/100 g
INACTIVE INGREDIENTS: WATER

ACTIVE INGREDIENT

75% Alcohol

PURPOSE

Antiseptic

INDICATIONS AND USAGE

Used for antibacterial hand skin.

WARNINGS

For external use only. Flammable. Keep away from fire.

DO NOT USE

• Keep away from fire.

• Do not wipe your eyes.

• Do not throw into the toilet (not soluble in water).

WHEN USING

• Please wait until the alcohol has completely evaporated after wiping.

• Before use, check whether the packaging is intact. Do not use if it is damaged.

Stop use and ask a doctor for those with alcohol allergy or sensitive skin.

Keep out of reach of children.

STORAGE AND HANDLING

• Store between 15-30℃ (59-86℉)

• Avoid freezing and excessive heat above 40℃ (104℉)

INACTIVE INGREDIENT

RO Water

DOSAGE AND ADMINISTRATION

Use it as needed following the usage instructions.